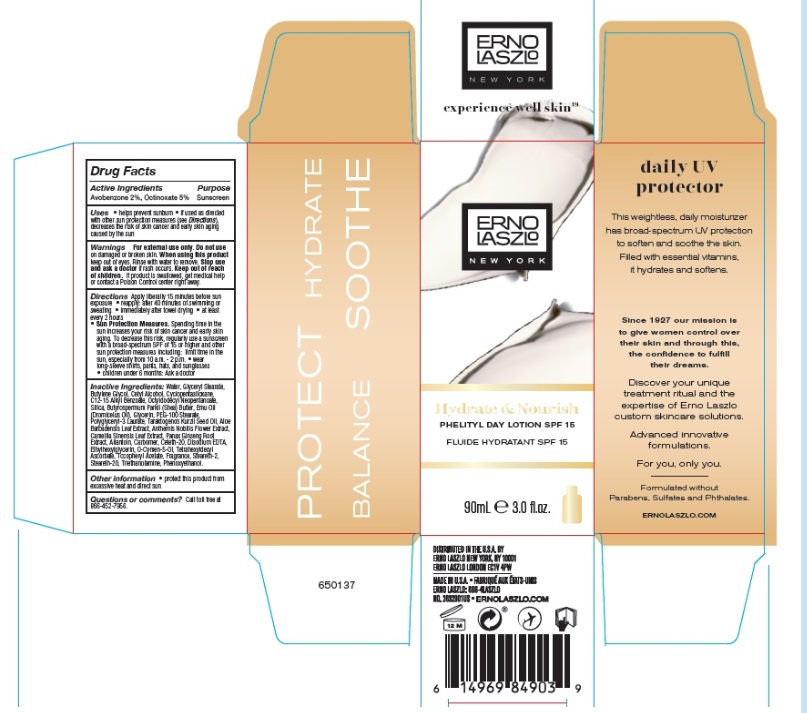 DRUG LABEL: Phelityl Day  SPF 15
NDC: 57913-2832 | Form: LOTION
Manufacturer: Erno Laszlo, Inc.
Category: otc | Type: HUMAN OTC DRUG LABEL
Date: 20241015

ACTIVE INGREDIENTS: AVOBENZONE 20 mg/1 mL; OCTINOXATE 50 mg/1 mL
INACTIVE INGREDIENTS: WATER; GLYCERYL MONOSTEARATE; BUTYLENE GLYCOL; CETYL ALCOHOL; CYCLOMETHICONE 5; ALKYL (C12-15) BENZOATE; OCTYLDODECYL NEOPENTANOATE; SILICON DIOXIDE; SHEA BUTTER; EMU OIL; GLYCERIN; PEG-100 STEARATE; MYRISTYL ALCOHOL; COCO GLUCOSIDE; ETHYLHEXYLGLYCERIN; DIMETHICONE; HYDNOCARPUS KURZII SEED OIL; ALOE VERA LEAF; CHAMAEMELUM NOBILE FLOWER; GREEN TEA LEAF; ASIAN GINSENG; ALLANTOIN; CETETH-20; EDETATE DISODIUM; O-CYMEN-5-OL; TETRAHEXYLDECYL ASCORBATE; .ALPHA.-TOCOPHEROL ACETATE; STEARETH-2; STEARETH-20; TROLAMINE; PHENOXYETHANOL

Phelityl Day SPF 15

Drug Facts

Active Ingredients

Avobenzone 2%, Octinoxate 5%

Purpose

Sunscreen

Uses

- helps prevent sunburn
- if used as directed with other sun protection measures (see Directions), decreases the risk of skin cancer and early skin aging caused by the sun

Warnings

For external use only.

Do not useon damaged or broken skin.

WHEN USING

When using this productkeep out of eyes. Rinse with water to remove.

Stop use and ask a doctorif rash occurs.

Keep out of reach of children.If product is swallowed, get medical help or contact a Poison Control center right away.

Directions

Apply liberally 15 minutes before sun exposure

- reapply: after 40 minutes of swimming or sweating
- immediately after towel drying
- at least every 2 hours
- Sun Protection Measures.Spending time in the sun increases your risk of skin cancer and early skin aging. To decrease this risk, regularly use a sunscreen with a broad spectrum SPF of 15 or higher and other sun protection measures including: limit time in the sun, especially from 10 a.m. - 2 p.m.
  - wear long-sleeve shirts, pants, hats, and sunglasses
  - children under 6 months: Ask a doctor

Inactive Ingredients

Water, Glyceryl Stearate, Butylene Glycol, Cetyl Alcohol, Cyclopentasiloxane, C12-15 Alkyl Benzoate, Octyldodecyl Neopentanoate, Silica, Butyrospermum Parkii (Shea) Butter, Emu Oil, Glycerin, PEG-100 Stearate, Polyglyceryl-3 Laurate, Taraktogenos Kurzii Seed Oil, Aloe Barbadensis Leaf Extract, Anthemis Nobilis Flower Extract, Camellia Sinensis Leaf Extract, Panax Ginseng Root Extract, Allantoin, Carbomer, Ceteth-20, Disodium EDTA, Ethylhexylglycerin, O-Cymen-5-Ol, Tetrahexyldecyl Ascorbate, Tocopheryl Acetate, Fragrance, Steareth-2, Steareth-20, Triethanolamine, Phenoxyethanol.

Other information

- protect this product from excessive heat and direct sun

Questions or comments?

Call toll free at 866-452-7956.

DISTRIBUTED IN U.S.A. BY
ERNO LASZLO NEW YORK, NY 10001